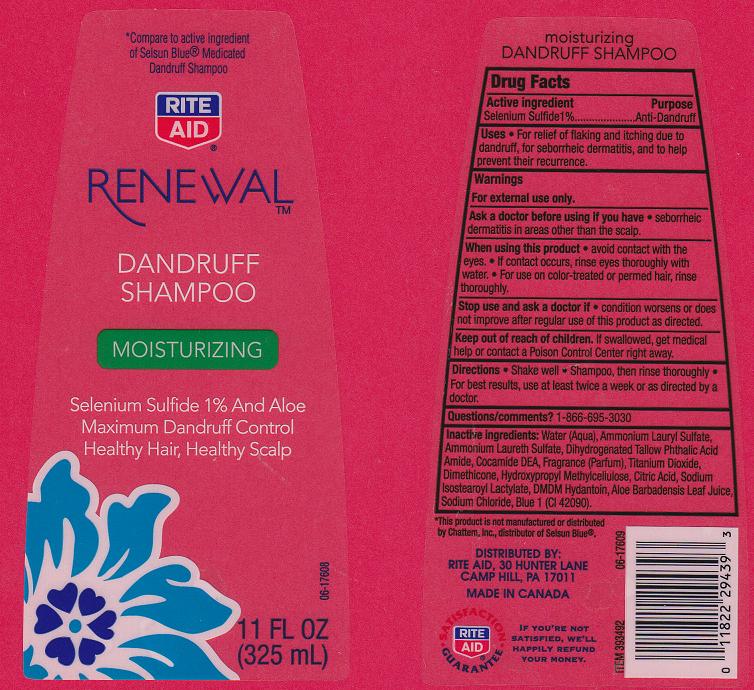 DRUG LABEL: Rite Aid Moisturizing Dandruff
NDC: 11822-6111 | Form: SHAMPOO
Manufacturer: Rite Aid Corporation
Category: otc | Type: HUMAN OTC DRUG LABEL
Date: 20120322

ACTIVE INGREDIENTS: SELENIUM SULFIDE 1 mL/100 mL
INACTIVE INGREDIENTS: WATER; AMMONIUM LAURYL SULFATE; AMMONIUM LAURETH-2 SULFATE; COCO DIETHANOLAMIDE; TITANIUM DIOXIDE; DIMETHICONE; HYPROMELLOSE 2208 (100 MPA.S); CITRIC ACID MONOHYDRATE; SODIUM ISOSTEAROYL LACTYLATE; DMDM HYDANTOIN; ALOE VERA LEAF; SODIUM CITRATE; SODIUM CHLORIDE; FD&C BLUE NO. 1

Drug Facts

Active Ingredient

Selenium Sulfide 1%

Purpose

Anti-Dandruff

Uses

For relief of flaking and itching due to dandruff, for seborrheic dermatitis, and to help prevent their recurrence.

Warnings

For external use only

Ask a doctor before using if you have

seborrheic dermatitis in areas other than the scalp.

When using this product

avoid contact with the eyes. If contact occurs, rinse eyes thoroughly with water. For use on color-treated or permed hair, rinse thoroughly.

Stop use and ask a doctor if

condition worsens or does not improve after regular use of this product as directed

Keep out of reach of children

If swallowed, get medical help or contact a Poison Control Center right away.

Directions

- Shake well. Shampoo, then rinse thoroughly.
- For best results, use at least twice a week or as directed by a doctor.

Questions/Comments?

1 - 866 - 695 - 3030

Inactive Ingredients:

Water (Aqua), Ammonium Lauryl Sulfate, Ammonium Laureth Sulfate, Dihydrogenated Tallow Phthalic Acid Amide, Cocamide DEA, Fragrance (Parfum), Titanium Dioxide, Dimethicone, Hydroxypropyl Methylcellulose, Citric Acid, Sodium Isostearoyl Lactylate, DMDM Hydantoin, Aloe Barbadensis Leaf Juice, Sodium Citrate, Sodium Chloride, Blue 1 (CI 42090)